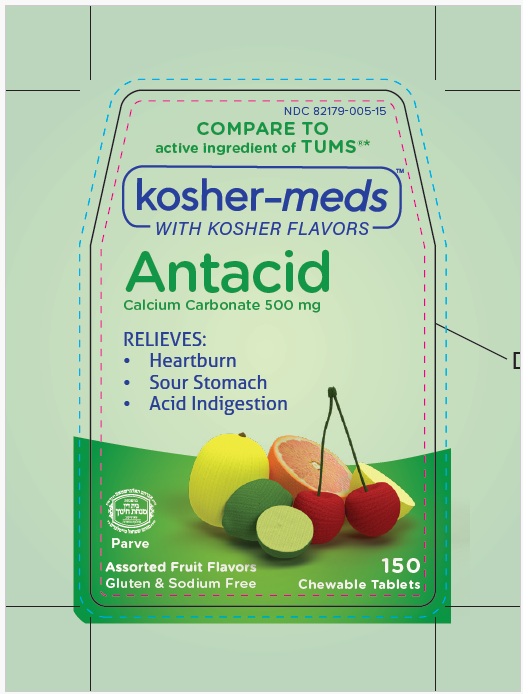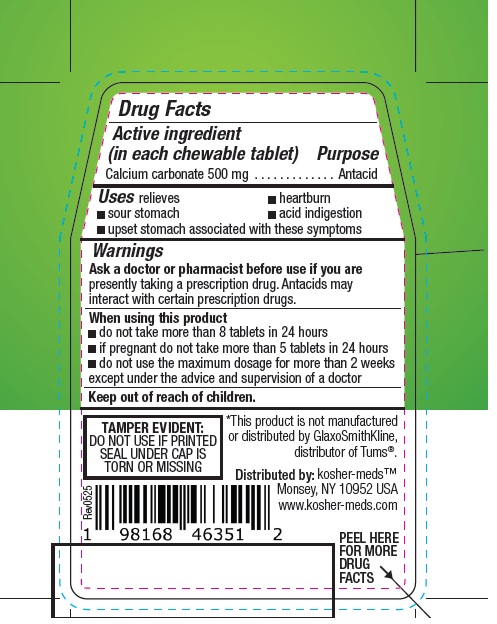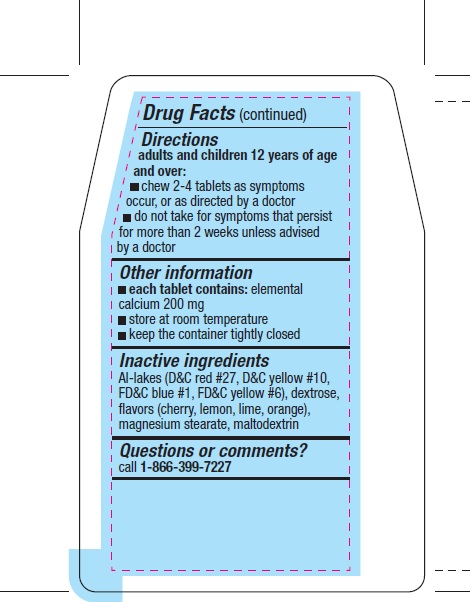 DRUG LABEL: KOSHER MEDS antacid
NDC: 82179-005 | Form: TABLET, CHEWABLE
Manufacturer: Mollec Inc
Category: otc | Type: HUMAN OTC DRUG LABEL
Date: 20250701

ACTIVE INGREDIENTS: CALCIUM CARBONATE 500 mg/1 1
INACTIVE INGREDIENTS: D&C RED NO. 27; FD&C YELLOW NO. 6; DEXTROSE, UNSPECIFIED FORM; MAGNESIUM STEARATE; MALTODEXTRIN; D&C YELLOW NO. 10; FD&C BLUE NO. 1

Active ingredient

Calcium carbonate 500 mg (in each chewable tablet)

Purpose

Antacid

Uses

relieves

- heartburn
- sour stomach
- acid indigestion
- upset stomach associated with these symptoms

Warnings

Ask a doctor or pharmacist before use if you arepresently taking a prescription drug. Antacids may interact with certain prescription drugs.

When using this product

- do not take more than 8 tablets in 24 hours
- if pregnant do not take more than 5 tablets in 24 hours
- do not use the maximum dosage for more than 2 weeks except under the advice and supervision of a doctor

Keep out of reach of children.

Directions

adults and children 12 years of age and over:

- chew 2-4 tablets as symptoms occur, or as directed by a doctor
- do not take for symptoms that persist for more than 2 weeks unless advised by a doctor

Other information

- each tablet contains: elemental calcium 200 mg
- store at room temperature
- keep the container tightly closed

Inactive ingredients

Al-lakes (D&C red #27, D&C yellow #10, FD&C blue #1, FD&C yellow #6), dextrose, flavors (cherry, lemon, lime, orange), magnesium stearate, maltodextrin

Questions or comments?

call 1-866-399-7227